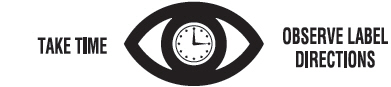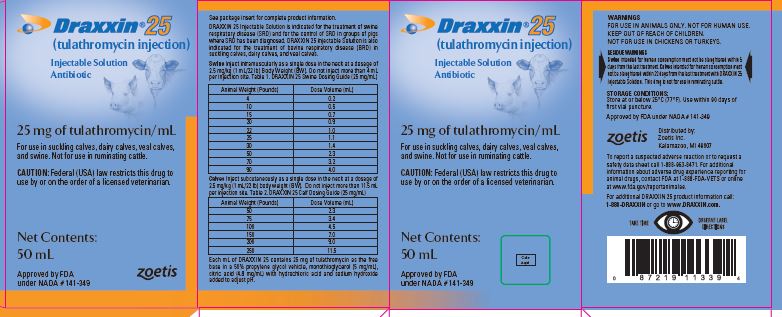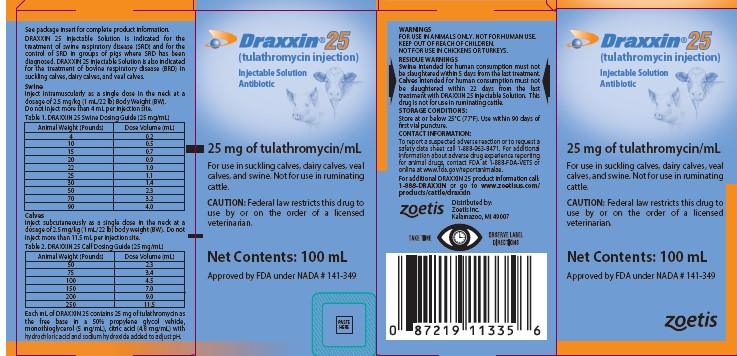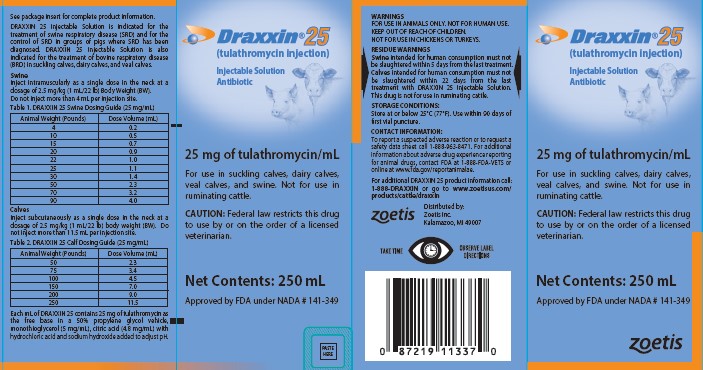 DRUG LABEL: Draxxin 25
NDC: 54771-8725 | Form: INJECTION
Manufacturer: Zoetis Inc.
Category: animal | Type: PRESCRIPTION ANIMAL DRUG LABEL
Date: 20260127

ACTIVE INGREDIENTS: TULATHROMYCIN 25 mg/1 mL

Draxxin® 25
(tulathromycin injection)
Injectable Solution

Antibiotic
25 mg of tulathromycin/mL

For use in suckling calves, dairy calves, veal calves, and swine. Not for use in ruminating cattle.

CAUTION

Federal law restricts this drug to use by or on the order of a licensed veterinarian.

DESCRIPTION

DRAXXIN 25 Injectable Solution is a ready-to-use sterile parenteral preparation containing tulathromycin, a semi-synthetic macrolide antibiotic of the subclass triamilide. Each mL of DRAXXIN 25 contains 25 mg of tulathromycin as the free base in a 50% propylene glycol vehicle, monothioglycerol (5 mg/mL), citric acid (4.8 mg/mL) with hydrochloric acid and sodium hydroxide added to adjust pH. DRAXXIN 25 consists of an equilibrated mixture of two isomeric forms of tulathromycin in a 9:1 ratio.

INDICATIONS

Swine

DRAXXIN 25 Injectable Solution is indicated for the treatment of swine respiratory disease (SRD) associated with Actinobacillus pleuropneumoniae, Pasteurella multocida, Bordetella bronchiseptica, Haemophilus parasuis, and Mycoplasma hyopneumoniae; and for the control of SRD associated with Actinobacillus pleuropneumoniae, Pasteurella multocida, and Mycoplasma hyopneumoniae in groups of pigs where SRD has been diagnosed.

Suckling Calves, Dairy Calves, and Veal Calves

BRD - DRAXXIN 25 Injectable Solution is indicated for the treatment of bovine respiratory disease (BRD) associated with Mannheimia haemolytica, Pasteurella multocida, Histophilus somni, and Mycoplasma bovis.

DOSAGE AND ADMINISTRATION

Swine

Inject intramuscularly as a single dose in the neck at a dosage of 2.5 mg/kg (1 mL/22 lb) Body Weight (BW). Do not inject more than 4 mL per injection site.

Table 1. DRAXXIN 25 Swine Dosing Guide (25 mg/mL)
Animal Weight (Pounds) | Dose Volume (mL)
4 | 0.2
10 | 0.5
15 | 0.7
20 | 0.9
22 | 1.0
25 | 1.1
30 | 1.4
50 | 2.3
70 | 3.2
90 | 4.0

Calves

Inject subcutaneously as a single dose in the neck at a dosage of 2.5 mg/kg (1 mL/22 lb) body weight (BW). Do not inject more than 11.5 mL per injection site.

Table 2. DRAXXIN 25 Calf Dosing Guide (25 mg/mL)

Animal Weight (Pounds) | Dose Volume (mL)
50 | 2.3
75 | 3.4
100 | 4.5
150 | 7.0
200 | 9.0
250 | 11.5

CONTRAINDICATIONS

The use of DRAXXIN 25 Injectable Solution is contraindicated in animals previously found to be hypersensitive to the drug.

WARNINGS

FOR USE IN ANIMALS ONLY. NOT FOR HUMAN USE.
KEEP OUT OF REACH OF CHILDREN.
NOT FOR USE IN CHICKENS OR TURKEYS.

RESIDUE WARNINGS

Swine

Swine intended for human consumption must not be slaughtered within 5 days from the last treatment.

Calves

Calves intended for human consumption must not be slaughtered within 22 days from the last treatment with DRAXXIN 25 Injectable Solution. This drug is not for use in ruminating cattle.

PRECAUTIONS

Swine

The effects of Draxxin 25 Injectable Solution on porcine reproductive performance, pregnancy, and lactation have not been determined. Intramuscular injection can cause a transient local tissue reaction that may result in trim loss of edible tissue at slaughter.

Cattle

The effects of Draxxin 25 Injectable Solution on bovine reproductive performance, pregnancy, and lactation have not been determined. Subcutaneous injection can cause a transient local tissue reaction that may result in trim loss of edible tissue at slaughter.

ADVERSE REACTIONS

Swine

In one field study, one out of 40 pigs treated with DRAXXIN Injectable Solution (100 mg/mL) at 2.5 mg/kg BW exhibited mild salivation that resolved in less than four hours.

Calves

In one BRD field study, two calves treated with DRAXXIN Injectable Solution (100 mg/mL) at 2.5 mg/kg BW exhibited transient hypersalivation. One of these calves also exhibited transient dyspnea, which may have been related to pneumonia.

Post Approval Experience

The following adverse events are based on post approval adverse drug experience reporting for DRAXXIN Injectable Solution (100 mg/mL). Not all adverse events are reported to the FDA CVM. It is not always possible to reliably estimate the adverse event frequency or establish a causal relationship to product exposure using these data. The following adverse events are listed in decreasing order of reporting frequency in cattle: Injection site reactions and anaphylaxis/anaphylactoid reactions. For a complete listing of adverse reactions for DRAXXIN Injectable Solution or DRAXXIN 25 Injectable Solution reported to the CVM see: http://www.fda.gov/AnimalVeterinary.

CLINICAL PHARMACOLOGY

At physiological pH, tulathromycin (a weak base) is approximately 50 times more soluble in hydrophilic than lipophilic media. This solubility profile is consistent with the extracellular pathogen activity typically associated with the macrolides.1 Markedly higher tulathromycin concentrations are observed in the lung parenchyma as compared to the plasma, and these elevated concentrations can remain in lung tissue for several days beyond that which can be measured in the plasma. However the clinical relevance of these elevated lung concentrations is undetermined.

As a class, macrolides tend to be primarily bacteriostatic, but may be bactericidal against some pathogens.^2 When acting as a cidal compound, they tend to exhibit concentration independent killing; the rate of bacterial eradication does not change once serum drug concentrations reach 2 to 3 times the minimum inhibitory concentration (MIC) of the targeted pathogen. Under these conditions, the time that serum concentrations remain above the MIC becomes the major determinant of antimicrobial activity. Macrolides also exhibit a post-antibiotic effect (PAE), the duration of which tends to be both drug and pathogen dependent. In general, by increasing the macrolide concentration and the exposure time, the PAE will increase to some maximal duration.^3 Tulathromycin is eliminated from the body primarily unchanged via biliary excretion.

^1 Carbon, C. 1998. Pharmacodynamics of Macrolides, Azalides, and Streptogramins: Effect on Extracellular Pathogens. Clin. Infect. Dis., 27:28-32.

^2 Nightingale, C.J. 1997. Pharmacokinetics and Pharmacodynamics of Newer Macrolides. Pediatr. Infect. Dis. J., 16:438-443.

^3 Andes D, Anon J, Jacobs MR, Craig WA. (2004). Application of pharmacokinetics and pharmacodynamics to antimicrobial therapy of respiratory tract infections. Clin Lab Med., 24:477-502.

Swine

Following intramuscular (IM) administration to feeder pigs at a dosage of 2.5 mg/kg BW, tulathromycin is nearly completely absorbed, with peak plasma concentrations achieved within ~0.25 hr. The volume of distribution exceeds 15 L/kg, which is consistent with extensive tissue binding. This large distribution volume results in a long terminal elimination half- life (60 to 90 hours) despite a rapid systemic free drug clearance (187 mL/kg/hr). There are no gender differences in swine tulathromycin pharmacokinetics.

Comparative Bioavailability Summary

Despite slightly lower peak concentrations with DRAXXIN 25 Injectable Solution, a single IM dose of 2.5 mg tulathromycin/kg BW of either DRAXXIN Injectable Solution (100 mg/mL) or DRAXXIN 25 Injectable Solution (25 mg/mL) resulted in comparable tulathromycin total systemic exposure. Therefore, DRAXXIN 25 Injectable Solution is considered to be therapeutically equivalent to DRAXXIN Injectable Solution when administered to swine by IM injection at a dose of 2.5 mg tulathromycin/kg BW.

Calves

Following subcutaneous (SC) administration into the neck of feeder calves at a dosage of 2.5 mg/kg BW, tulathromycin is nearly completely absorbed, with peak plasma concentrations achieved within ~0.25 hr. The volume of distribution exceeds 11 L/kg4, which is consistent with extensive tissue binding. This large distribution volume results in a long terminal elimination half- life of more than 100 hours, despite a rapid systemic free drug clearance (170 mL/kg/hr). No pharmacokinetic differences are observed in castrated male versus female calves.

Comparative Bioavailability Summary

Despite lower peak concentrations with DRAXXIN 25 Injectable Solution, a single SC dose of 2.5 mg tulathromycin/kg BW of either DRAXXIN Injectable Solution (100 mg/mL) or DRAXXIN 25 Injectable Solution (25 mg/mL) resulted in comparable total systemic tulathromycin exposure. Therefore, DRAXXIN 25 Injectable Solution is considered to be therapeutically equivalent to DRAXXIN Injectable Solution when administered to calves by SC injection at a dose of 2.5 mg tulathromycin/kg BW.

^4 Clearance and volume estimates are based on intersubject comparisons of 2.5 mg/kg BW administered by either subcutaneous or intravenous injection.

MICROBIOLOGY

Swine

Tulathromycin has demonstrated in vitro activity against A. pleuropneumoniae, P. multocida, B. bronchiseptica, H. parasuis, and M. hyopneumoniae. The MICs of tulathromycin against indicated pathogens collected from field studies were determined using methods recommended by the Clinical and Laboratory Standards Institute (CLSI, M31-A and M31-A3). MICs for H. parasuis were determined using Veterinary Fastidious Medium and were incubated up to 48 hours at 35 to 37°C in a CO2-enriched atmosphere. These values are represented in Table 3, below.

Table 3. Tulathromycin minimum inhibitory concentration (MIC) values [The correlation between in vitro susceptibility data and clinical effectiveness is unknown.] for indicated pathogens isolated from field studies evaluating SRD in the U.S. and Canada.
Indicated pathogen | Date isolated | No. of isolates | MIC50 [The lowest MIC to encompass 50% and 90% of the most susceptible isolates, respectively.] (μg/mL) | MIC90 (μg/mL) | MIC range (μg/mL)
Actinobacillus pleuropneumoniae | 2000-2002 2007-2008 | 135 88 | 16 16 | 32 16 | 16 to 32 4 to 32
Haemophilus parasuis | 2000-2002 | 31 | 1 | 2 | 0.25 to > 64
Pasteurella multocida | 2000-2002 2007-2008 | 55 40 | 1 1 | 2 2 | 0.5 to > 64 ≤ 0.03 to 2
Bordetella bronchiseptica | 2000-2002 | 42 | 4 | 8 | 2 to 8

*The correlation between in vitro susceptibility data and clinical effectiveness is unknown.

** The lowest MIC to encompass 50% and 90% of the most susceptible isolates, respectively

Calves

Tulathromycin has demonstrated in vitro activity against M. haemolytica, P. multocida, H. somni, and M. bovis, four pathogens associated with BRD. The MICs of tulathromycin against indicated pathogens collected from field studies using DRAXXIN Injectable Solution (100 mg/mL) were determined using methods recommended by the CLSI (M31-A2). These values are represented in Table 4, below.

Table 4. Tulathromycin minimum inhibitory concentration (MIC) values for indicated pathogens isolated from field studies evaluating BRD in the U.S.
Indicated pathogen | Date isolated | No. of isolates | MIC50 (μg/mL) | MIC90 (μg/mL) | MIC range (μg/mL)
Manneheimia haemolytica | 1999 | 642 | 2 | 2 | 0.5 to 64
Pasteurella multocida | 1999 | 221 | 0.5 | 1 | 0.25 to 64
Histophilus somni | 1999 | 36 | 4 | 4 | 1 to 4
Mycoplasma bovis | 1999 | 43 | 0.125 | 1 | ≤0.063 to > 64

* The correlation between in vitro susceptibility data and clinical effectiveness is unknown.

** The lowest MIC to encompass 50% and 90% of the most susceptible isolates, respectively.

EFFECTIVENESS

Swine

Plasma concentrations of tulathromycin administered as DRAXXIN Injectable Solution (100 mg/mL) or as DRAXXIN 25 Injectable Solution were demonstrated to be therapeutically equivalent (see CLINICAL PHARMACOLOGY, Comparative Bioavailability Summary). Therefore effectiveness studies conducted with DRAXXIN Injectable Solution (100 mg/mL) support the effectiveness for DRAXXIN 25 Injectable Solution.

In a multi-location field study to evaluate the treatment of naturally occurring SRD, 266 pigs were treated with DRAXXIN Injectable Solution (100 mg/mL). Responses to treatment were compared to saline-treated controls. Success was defined as a pig with normal attitude, normal respiration, and rectal temperature of < 104°F on Day 7. The treatment success rate was significantly greater (P ≤ 0.05) in DRAXXIN-treated pigs (70.5%) compared to saline-treated pigs (46.1%). M. hyopneumoniae was isolated from 106 saline-treated and non-treated sentinel pigs in this study.

Two induced infection model studies were conducted to confirm the effectiveness of DRAXXIN Injectable Solution (100 mg/mL) against M. hyopneumoniae. Ten days after inoculation intranasally and intratracheally with a field strain of M. hyopneumoniae, 144 pigs were treated with either DRAXXIN (2.5 mg/kg BW) intramuscularly or an equivalent volume of saline. Pigs were euthanized and necropsied 10 days post-treatment. The mean percentage of gross pneumonic lung lesions was statistically significantly lower (P < 0.0001) for DRAXXIN-treated pigs than for saline-treated pigs in both studies (8.52% vs. 23.62% and 11.31% vs. 26.42%).

The effectiveness of DRAXXIN Injectable Solution (100 mg/mL) for the control of SRD was evaluated in a multi-location natural infection field study. When at least 15% of the study candidates showed clinical signs of SRD, all pigs were enrolled and treated with DRAXXIN (226 pigs) or saline (227 pigs). Responses to treatment were evaluated on Day 7. Success was defined as a pig with normal attitude, normal respiration, and rectal temperature of < 104°F. The treatment success rate was significantly greater (P < 0.05) in DRAXXIN-treated pigs compared to saline-treated pigs (59.2% vs. 41.2%).

Calves

Plasma concentrations of tulathromycin administered as DRAXXIN Injectable Solution (100 mg/mL) or as DRAXXIN 25 Injectable Solution were demonstrated to be therapeutically equivalent (see CLINICAL PHARMACOLOGY, Comparative Bioavailability Summary). Therefore effectiveness studies conducted with DRAXXIN Injectable Solution (100 mg/mL) support the effectiveness for DRAXXIN 25 Injectable Solution.

BRD - In a multi-location field study, 314 calves with naturally occurring BRD were treated with DRAXXIN Injectable Solution (100 mg/mL). Responses to treatment were compared to saline-treated controls. A cure was defined as a calf with normal attitude/activity, normal respiration, and a rectal temperature of ≤104°F on Day 14. The cure rate was significantly higher (P ≤ 0.05) in DRAXXIN-treated calves (78%) compared to saline-treated calves (24%). There were two BRD-related deaths in the DRAXXIN-treated calves compared to nine BRD-related deaths in the saline-treated calves.

Fifty-two DRAXXIN Injectable Solution (100 mg/mL)-treated calves and 27 saline-treated calves from the multi-location field BRD treatment study had Mycoplasma bovis identified in cultures from pre-treatment nasopharyngeal swabs. Of the 52 DRAXXIN-treated calves, 37 (71.2%) calves were categorized as cures and 15 (28.8%) calves were categorized as treatment failures. Of the 27 saline-treated calves, 4 (14.8%) calves were categorized as cures and 23 (85.2%) calves were treatment failures.

A Bayesian meta-analysis was conducted to compare the BRD treatment success rate in young calves (calves weighing 250 lbs or less and fed primarily a milk-based diet) treated with DRAXXIN Injectable Solution (100 mg/mL) to the success rate in older calves (calves weighing more than 250 lbs and fed primarily a roughage and grain-based diet) treated with DRAXXIN. The analysis included data from four BRD treatment effectiveness studies conducted for the approval of DRAXXIN Injectable Solution (100 mg/mL) in the U.S. and nine contemporaneous studies conducted in Europe. The analysis showed that the BRD treatment success rate in young calves was at least as good as the BRD treatment success rate in older calves. As a result, DRAXXIN Injectable Solution (100 mg/mL) was considered effective for the treatment of BRD associated with M. haemolytica, P. multocida, H. somni, and M. bovis in suckling calves, dairy calves, and veal calves.

Two induced infection model studies were conducted to confirm the effectiveness of DRAXXIN Injectable Solution (100 mg/mL) against Mycoplasma bovis. A total of 166 calves were inoculated intratracheally with field strains of Mycoplasma bovis. When calves became pyrexic and had abnormal respiration scores, they were treated with either DRAXXIN (2.5 mg/kg BW) subcutaneously or an equivalent volume of saline. Calves were observed for signs of BRD for 14 days post-treatment, then were euthanized and necropsied. In both studies, mean lung lesion percentages were statistically significantly lower in the DRAXXIN-treated calves compared with saline-treated calves (11.3% vs. 28.9%, P = 0.0001 and 15.0% vs. 30.7%, P < 0.0001).

ANIMAL SAFETY

Swine

Plasma concentrations of tulathromycin administered as DRAXXIN Injectable Solution (100 mg/mL) or as DRAXXIN 25 Injectable Solution were demonstrated to be therapeutically equivalent (see CLINICAL PHARMACOLOGY, Comparative Bioavailability Summary). Therefore systemic target animal safety studies conducted with DRAXXIN Injectable Solution support the systemic safety for DRAXXIN 25 Injectable Solution.

Safety studies were conducted in pigs receiving a single intramuscular dose of 25 mg/kg BW, or 3 weekly intramuscular doses of 2.5, 7.5, or 12.5 mg/kg BW (both studies utilized DRAXXIN Injectable Solution (100 mg/mL)). In all groups, transient indications of pain after injection were seen, including restlessness and excessive vocalization. Tremors occurred briefly in one animal receiving 7.5 mg/ kg BW. Discoloration and edema of injection site tissues and corresponding histopathologic changes were seen in animals at all dosages and resolved over time. No other drug-related lesions were observed macroscopically or microscopically.

Sixteen growing pigs were injected with either saline or DRAXXIN 25 Injectable Solution as a single injection of 4 mL. Injection site observations included two instances of erythema in the DRAXXIN 25-treated group on Day 1 post-injection. No heat, sensitivity, firmness, necrosis, drainage, or swelling was observed at any injection sites in either treatment group. The gross and microscopic findings in the DRAXXIN 25-treated group were consistent with inflammatory changes induced by injections and were considered to be mild or moderate with progression to macroscopic resolution by Day 28 post-injection and microscopic resolution by Day 42 post-injection.

Calves

Plasma concentrations of tulathromycin administered as DRAXXIN Injectable Solution (100 mg/mL) or as DRAXXIN 25 Injectable Solution were demonstrated to be therapeutically equivalent (see CLINICAL PHARMACOLOGY, Comparative Bioavailability Summary). Therefore effectiveness studies conducted with DRAXXIN Injectable Solution support the effectiveness for DRAXXIN 25 Injectable Solution.

A safety study was conducted in feeder calves receiving DRAXXIN Injectable Solution (100 mg/mL) as a single subcutaneous dose of 25 mg/kg BW, or 3 weekly subcutaneous doses of 2.5, 7.5, or 12.5 mg/kg BW. In all groups, transient indications of pain after injection were seen, including head shaking and pawing at the ground. Injection site swelling, discoloration of the subcutaneous tissues at the injection site and corresponding histopathologic changes were seen in animals in all dosage groups. These lesions showed signs of resolving over time. No other drug-related lesions were observed macroscopically or microscopically.

An exploratory study was conducted in feeder calves receiving DRAXXIN Injectable Solution (100 mg/mL) as a single subcutaneous dose of 10, 12.5, or 15 mg/kg BW. Macroscopically, no lesions were observed. Microscopically, minimal to mild myocardial degeneration was seen in one of six calves administered 12.5 mg/kg BW and two of six calves administered 15 mg/kg BW.

A safety study was conducted in preruminant calves 13 to 27 days of age receiving DRAXXIN Injectable Solution (100 mg/mL) at 2.5 mg/kg BW or 7.5 mg/kg BW once subcutaneously. With the exception of minimal to mild injection site reactions, no drug-related clinical signs or other lesions were observed macroscopically or microscopically.

Sixteen growing cattle were injected with either saline (eight animals) as a single injection of 11.5 mL or DRAXXIN 25 Injectable Solution (eight animals) as a single injection of either 2.5 mg/kg BW or a dose volume of 11.5 mL (whichever volume was higher). One calf in the DRAXXIN 25-treated group was observed to have firmness at the injection site for a single day. Two DRAXXIN 25-treated calves exhibited injection site swelling. In one calf, the swelling resolved within 48 hours. In the other calf, the swelling was observed over a three-day period, after which the calf underwent a scheduled necropsy, preventing further injection site observations. No injection site swelling was observed in saline-treated animals. At necropsy, three of the saline-treated calves and five of the DRAXXIN 25-treated calves had altered tissue present at the injection site. The gross and microscopic findings in the DRAXXIN 25-treated group were consistent with inflammatory changes induced by injections, were considered to be mild to marked, and progressed to macroscopic resolution and microscopic resolution by Day 42 post-injection.

STORAGE CONDITIONS:

Store at or below 25°C (77°F). Use within 90 days of first vial puncture.

HOW SUPPLIED

DRAXXIN 25 Injectable Solution is available in the following package sizes:

50 mL vial
100 mL vial
250 mL vial

Approved by FDA under NADA # 141-349

zoetis

Distributed by:
Zoetis Inc.
Kalamazoo, MI 49007

CONTACT INFORMATION

To report a suspected adverse reaction or to request a safety data sheet call 1-888-963-8471. For additional information about adverse drug experience reporting for animal drugs, contact FDA at 1-888-FDA-VETS or online at www.fda.gov/reportanimalae.
For additional DRAXXIN 25 product information call: 1-888-DRAXXIN or go to www.zoetisus.com/products/cattle/draxxin
Revised: March 2025

PRINCIPAL DISPLAY PANEL - 50 mL Vial Carton

50 mL Carton

PRINCIPAL DISPLAY PANEL - 100 mL Vial Carton

40051463 100 mL

PRINCIPAL DISPLAY PANEL - 250 mL Vial Carton

40051465 250 mL Vial